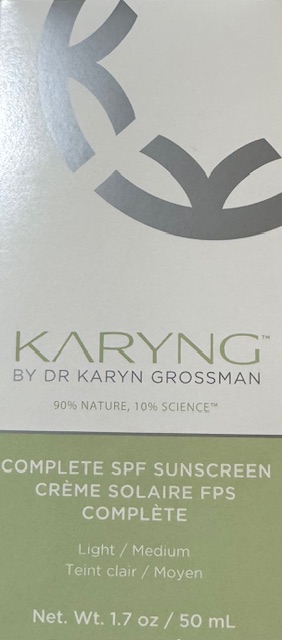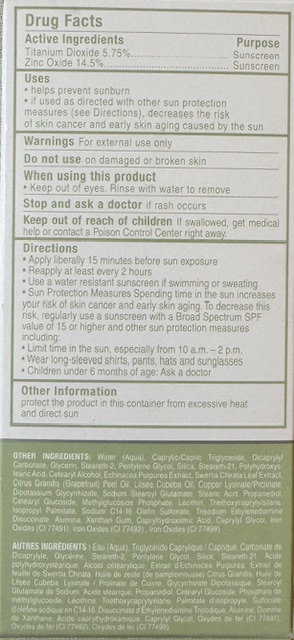 DRUG LABEL: KARYNG Complete SPF Sunscreen
NDC: 85321-001 | Form: CREAM
Manufacturer: Karyng LLC
Category: otc | Type: HUMAN OTC DRUG LABEL
Date: 20250422

ACTIVE INGREDIENTS: ZINC OXIDE 14.5 g/100 g; TITANIUM DIOXIDE 5.75 g/100 g
INACTIVE INGREDIENTS: WATER; DIPOTASSIUM GLYCYRRHIZATE; ECHINACEA PURPUREA; SILICON DIOXIDE; TRISODIUM ETHYLENEDIAMINE DISUCCINATE; SODIUM C14-16 OLEFIN SULFONATE; GLYCERIN; CETEARYL GLUCOSIDE; TRIETHOXYCAPRYLYLSILANE; STEARETH-2; STEARETH-21; CAPRYLHYDROXAMIC ACID; CAPRYLYL GLYCOL; CITRUS GRANDIS (GRAPEFRUIT) PEEL OIL; PENTYLENE GLYCOL; XANTHAN GUM; STEARIC ACID; ISOPROPYL PALMITATE; CETEARYL ALCOHOL; CAPRYLIC/CAPRIC TRIGLYCERIDE; POLYHYDROXYSTEARIC ACID (2300 MW); PROPANEDIOL; SODIUM STEAROYL GLUTAMATE; ALUMINA; DICAPRYLYL CARBONATE

KARYNG Complete SPF Sunscreen (Light/Medium)

ACTIVE INGREDIENT

Titanium Dioxide 5.75%

Zinc Oxide 14.5%

PURPOSE

Sunscreen

WARNINGS

For external use only.

WHEN USING

Do not get into eyes. Rinse with water to remove.

Stop use and ask a doctor if rash or irritation occurs.

Keep out of reach of children.If swallowed, get medical help or contact a Poison Control Center right away.

Directions:

Apply liberally 15 minutes before sun exposure.

Reapply after at least every 2 hours

Use a water resistant sunscreen if swimming or sweating

Sun protection measures spending time in the sun increases your risk of skin cancer and early skin aging. To decrease this risk, regularly use a sunscreen with a broad spectrum SPF value of 15 or higher and other sun protection measures including:

Limit time in the sun, especially from 10am-2pm

Wear long-sleeved shirts, pants, hats and sunglasses

Children under six months of age, ask a doctor

USER SAFETY WARNINGS

Sun Alert. Limiting sun exposure, wearing protective clothing, and using suncreens may reduce the risks of skin aging, skin cancer, and other harmful effects of the sun.

OTHER SAFETY INFORMATION

Protect the product in this container from excessive heat and direct sun

INACTIVE INGREDIENT

Water (Aqua), Caprylic/Capric Triglyceride, Dicaprylyl Carbonate, Glycerin, Steareth-2, Pentylene Glycol, Silica, Steareth-21, Polyhydroxystearic Acid, Cetearyl Alcohol. Echinacea Purpurea Extract. Swertia Chirata Leaf Extract, Citrus Grandis (Grapefruit) Peel Oil, Litsea Cubeba Oil, Copper Lysinate/Prolinate, Dipotassium Glycyrrhizate, Sodium Stearoyl Glutamate, Stearic Acid, Propanediol Cetearyl Glucoside, Methylglucoside Phosphate, Lecithin, Triethoxycaprylylsilane, Isopropyl Palmitate, Sodium C14-16 Olefin Sulfonate, Trisodium Ethylenediamine Disuccinate. Alumina, Xanthan Gum, Caprylhydroxamic Acid, Caprylyl Glycol, Iron Oxides (CI 77491), Iron Oxides (CI 77492), Iron Oxides (CI 77499).

INDICATIONS AND USAGE

Helps prevent sunburn. If used as directed with other sun protection measures (See Sun Alert), decreases the risk of skin cancer and early skinaging by the sun.